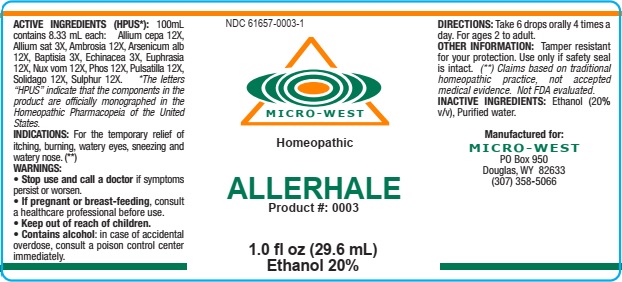 DRUG LABEL: Allerhale
NDC: 61657-0003 | Form: LIQUID
Manufacturer: White Manufacturing Inc. DBA Micro West
Category: homeopathic | Type: HUMAN OTC DRUG LABEL
Date: 20210121

ACTIVE INGREDIENTS: ARSENIC TRIOXIDE 12 [hp_X]/30 mL; PHOSPHORUS 12 [hp_X]/30 mL; STRYCHNOS NUX-VOMICA SEED 12 [hp_X]/30 mL; ONION 12 [hp_X]/30 mL; PULSATILLA VULGARIS 12 [hp_X]/30 mL; SULFUR 12 [hp_X]/30 mL; EUPHRASIA STRICTA 12 [hp_X]/30 mL; SOLIDAGO VIRGAUREA FLOWERING TOP 12 [hp_X]/30 mL; ECHINACEA, UNSPECIFIED 3 [hp_X]/30 mL; GARLIC 3 [hp_X]/30 mL; BAPTISIA TINCTORIA 3 [hp_X]/30 mL
INACTIVE INGREDIENTS: ALCOHOL

DRUG FACTS

ACTIVE INGREDIENTS

Allium cepa 12X

Allium sat 3X

Ambrosia 12X

Arsenicum alb 12X

Baptisia 3X

Echinacea 3X

Euphresia 12X

Nux vom 12X

Phosphorus 12X

Pulsatilla 12X

Solidago 12X

Sulphur

PURPOSE

ITCHING,BURNING, WATERY EYES, SNEEZING

KEEP OUT OF REACH OF CHILDREN

INDICATIONS

INDICATIONS: FOR THE TEMPORARY RELIEF OF ITCHING, BURNING, WATERY EYES, SNEEZING, AND WATERY NOSE

WARNING

WARNING:Stop use and call a doctor if symptoms persist or worsen. If pregnant or breast feeding, consult a healthcare professional. Contains alcohol: In case of accidental overdoseconsult a poison control center immediately

DIRECTIONS

DIRECTIONS:TAKE 6 DROPS ORALLY, 4 TIMES A DAY. FOR AGES 2 TO ADULT

INACTIVE INGREDIENT

ALCOHOL (20%V/V),PURIFIED WATER

MANUFACTURE

MANUFACTURED FOR MICRO WEST

DOUGLAS, WY 82633

1-307-358-5066

LABEL

NDC 61657-0003-1

MICRO-WEST

Homeopathic

ALLERHALE

Product #:0003

1.0 fl oz (29.6 mL)

Ethanol 20%